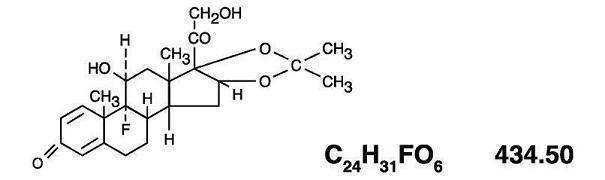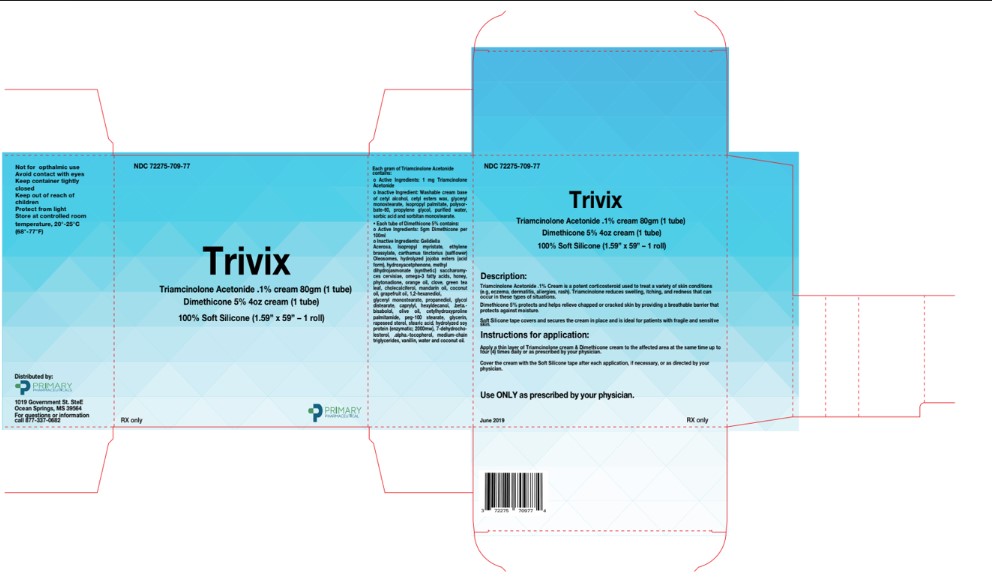 DRUG LABEL: Trivix
NDC: 72275-709 | Form: KIT | Route: TOPICAL
Manufacturer: Primary Pharmaceuticals, Inc.
Category: prescription | Type: HUMAN PRESCRIPTION DRUG LABEL
Date: 20190805

ACTIVE INGREDIENTS: TRIAMCINOLONE ACETONIDE 1 mg/1 g; DIMETHICONE 5 g/100 mL
INACTIVE INGREDIENTS: ISOPROPYL PALMITATE; POLYSORBATE 60; GLYCERIN; CETYL ESTERS WAX; PROPYLENE GLYCOL; WATER; GLYCERYL MONOSTEARATE; SORBIC ACID; CETYL ALCOHOL; SORBITAN MONOSTEARATE; GELIDIELLA ACEROSA; METHYL DIHYDROJASMONATE (SYNTHETIC); HONEY; ISOPROPYL MYRISTATE; HYDROLYZED JOJOBA ESTERS (ACID FORM); SACCHAROMYCES CEREVISIAE; OMEGA-3 FATTY ACIDS; PHYTONADIONE; ORANGE OIL; CHOLECALCIFEROL; ETHYLENE BRASSYLATE; RAPESEED STEROL; HYDROLYZED SOY PROTEIN (ENZYMATIC; 2000 MW); CORN OIL; GREEN TEA LEAF; CARTHAMUS TINCTORIUS SEED OLEOSOMES; .ALPHA.-TOCOPHEROL ACETATE, DL-; PEG-100 STEARATE; WATER; STEARIC ACID; OLIVE OIL; COCONUT OIL; GLYCERIN; HYDROXYACETOPHENONE; CLOVE; MANDARIN OIL; GRAPEFRUIT OIL; 1,2-HEXANEDIOL; GLYCERYL MONOSTEARATE; PROPANEDIOL; CETYLHYDROXYPROLINE PALMITAMIDE; GLYCOL DISTEARATE; CAPRYLYL GLYCOL; HEXYLDECANOL; .BETA.-BISABOLOL; 7-DEHYDROCHOLESTEROL; MEDIUM-CHAIN TRIGLYCERIDES; VANILLIN

Trivix

Triamcinolone Acetonide Cream USP (0.1%)

DESCRIPTION

The topical corticosteroids constitute a class of primarily synthetic steroids used as anti-inflammatory and antipruritic agents. Triamcinolone acetonide is a member of this class. Chemically triamcinolone acetonide is pregna-1, 4-diene-3, 20-dione, 9-flouro-11, 21-dihydroxy-16, 17-[(1-methylethylidene)bis(oxy)]-(11β16a). Its structural formula is:

Each gram of triamcinolone acetonide cream contains 1 mg triamcinolone acetonide USP in a cream base consisting of purified water, emulsifying wax, mineral oil, propylene glycol, sorbitol solution, cetyl palmitate, sorbic acid, and potassium sorbate.

CLINICAL PHARMACOLOGY

Topical corticosteroids share anti-inflammatory, anti-pruritic and vasoconstrictive actions. The
mechanism of anti-inflammatory activity of the topical corticosteroids is unclear. Various laboratory
methods, including vasoconstrictor assays, are used to compare and predict potencies and/or clinical
efficacies of the topical corticosteroids. There is some evidence to suggest that a recognizable
correlation exists between vasoconstrictor potency and therapeutic efficacy in man.
Pharmacokinetics -
The extent of percutaneous absorption of topical corticosteroids is determined by many factors
including the vehicle, the integrity of the epidermal barrier, and the use of occlusive dressings. Topical
corticosteroids can be absorbed from normal intact skin. Inflammation and/or other disease processes in
the skin increase percutaneous absorption. Occlusive dressings substantially increase the percutaneous
absorption of topical corticosteroids. Thus, occlusive dressings may be a valuable therapeutic adjunct
for treatment of resistant dermatoses (see DOSAGE AND ADMINISTRATION). Once absorbed
through the skin, topical corticosteroids are handled through pharmacokinetic pathways similar to
24 31 6
through the skin, topical corticosteroids are handled through pharmacokinetic pathways similar to
systemically administered corticosteroids. Corticosteroids are bound to plasma proteins in varying
degrees. Corticosteroids are metabolized primarily in the liver and are then excreted by the kidneys.
Some of the topical corticosteroids and their metabolites are also excreted into the bile.

INDICATIONS AND USAGE

Triamcinolone acetonide cream is indicated for the relief of the inflammatory and pruritic manifestations of corticosteroid-responsive dermatoses.

CONTRAINDICATIONS

Triamcinolone acetonide cream is contraindicated in those patients with a history of hypersensitivity to any of the components of the preparation.

PRECAUTIONS

General

Systemic absorption of topical corticosteroids has produced reversible hypothalamic-pituitary-adrenal (HPA) axis suppression, manifestations of Cushing's syndrome, hyperglycemia, and glucosuria in some patients.

Conditions which augment systemic absorption include the application of the more potent steroids, use over large surface areas, prolonged use, and the addition of occlusive dressings.

Therefore, patients receiving a large dose of a potent topical steroid applied to a large surface area or under an occlusive dressing should be evaluated periodically for evidence of HPA axis suppression by using the urinary free cortisol and ACTH stimulation tests. If HPA axis suppression is noted, an attempt should be made to withdraw the drug, to reduce the frequency of application, or to substitute a less potent steroid.

Recovery of HPA axis function is generally prompt and complete upon discontinuation of the drug. Infrequently, signs and symptoms of steroid withdrawal may occur, requiring supplemental systemic corticosteroids. Children may absorb proportionally larger amounts of topical corticosteroids and thus be more susceptible to systemic toxicity (See PRECAUTIONS-PEDIATRIC USE).

If irritation develops, topical corticosteroids should be discontinued and appropriate therapy instituted.

In the presence of dermatological infections, the use of an appropriate antifungal or antibacterial agent should be instituted. If a favorable response does not occur promptly, the corticosteroid should be discontinued until the infection has been adequately controlled.

Information for the Patient

Patients using topical corticosteroids should receive the following information and instructions.

1. This medication is to be used as directed by the physician. It is for external use only. Avoid contact with the eyes.
2. Patients should be advised not to use this medication for any disorder other than for which it was prescribed.
3. The treated skin area should not be bandaged or otherwise covered or wrapped as to be occlusive unless directed by the physician.
4. Patients should report any signs of local adverse reactions especially under occlusive dressing.
5. Parents of pediatric patients should be advised not to use tight-fitting diapers or plastic pants on a child being treated in the diaper area, as these garments may constitute occlusive dressings.

Laboratory Tests

The following tests may be helpful in evaluating the HPA axis suppression:

- Urinary free cortisol test
- ACTH stimulation test

Carcinogenesis, Mutagenesis, and Impairment of Fertility

Long-term animal studies have not been performed to evaluate the carcinogenic potential or the effect on fertility of topical corticosteroids.

Studies to determine mutagenicity with prednisolone and hydrocortisone have revealed negative results.

Pregnancy Category C

Corticosteroids are generally teratogenic in laboratory animals when administered systemically at relatively low dosage levels. The more potent corticosteroids have been shown to be teratogenic after dermal application in laboratory animals. There are not adequate and well-controlled studies in pregnant women on teratogenic effects from topically applied corticosteroids. Therefore, topical corticosteroids should be used during pregnancy only if the potential benefit justifies the potential risk to the fetus. Drugs of this class should not be used extensively on pregnant patients, in large amounts, or for prolonged periods of time.

Nursing Mothers

It is not known whether topical administration of corticosteroids could result in sufficient systemic absorption to produce detectable quantities in breast milk. Systemically administered corticosteroids are secreted into breast milk in quantities not likely to have a deleterious effect on the infant. Nevertheless, caution should be exercised when topical corticosteroids are administered to a nursing woman.

Pediatric Use

Pediatric patients may demonstrate greater susceptibility to topical corticosteroid-induced HPA axis suppression and Cushing's syndrome than mature patients because of a larger skin surface area to body weight ratio.

Hypothalamic-pituitary-adrenal (HPA) axis suppression, Cushings's syndrome and intracranial hypertension have been reported in children receiving topical corticosteroids. Manifestations of adrenal suppression in children include linear growth retardation, delayed weight gain, low plasma cortisol levels, and absence of response to ACTH stimulation. Manifestations of intracranial hypertension include bulging fontanelles, headaches, and bilateral papilledema.

Administration of topical corticosteroids to children should be limited to the least amount compatible with an effective therapeutic regimen. Chronic corticosteroid therapy may interfere with the growth and development of children.

ADVERSE REACTIONS

The following local adverse reactions are reported infrequently with topical corticosteroids, but may occur more frequently with the use of occlusive dressings. These reactions are listed in an approximate decreasing order of occurrence:

- Burning
- Itching
- Irritation
- Dryness
- Folliculitis
- Hypertrichosis
- Acneiform eruptions
- Hypopigmentation
- Perioral dermatitis
- Allergic contact dermatitis
- Maceration of the skin
- Secondary infection
- Skin Atrophy
- Striae
- Miliaria

DOSAGE AND ADMINISTRATION

Topical corticosteroids are generally applied to the affected area as a thin film from two to three times daily depending on the severity of the condition.

Occlusive dressing may be used for the management of psoriasis or recalcitrant conditions.

If an infection develops, the use of occlusive dressing should be discontinued and appropriate antimicrobial therapy instituted.

HOW SUPPLIED

Triamcinolone acetonide cream USP 0.1% is supplied in
80 g tube NDC 45802-064-36

Store at 59-86°F.

CAUTION: FEDERAL LAW PROHIBITS DISPENSING WITHOUT PRESCRIPTION.

MEDLINE REMEDY PHYTOPLEX SKIN REPAIR- (Dimethicone 5.0%)

Drug Facts

Active ingredient

Dimethicone 5.0%

Purpose

Skin Protectant

Uses

■ Temporarily protects and helps relieve chapped or cracked skin
■ Beneficial for face, hands, body and legs.

Warnings

For external use only

Do not use on ■ deep or puncture wounds ■ animal bites ■ serious burns

When using this product
avoid contact with eyes.

Stop use and ask a doctor if

condition worsens
symptoms last for more than 7 days or clear up and occur again within a few days

Keep out of reach of children.
If swallowed, get medical help or contact a Poison Control Center right away.

Directions

■ apply cream liberally as needed

Other information

■ protect from freezing ■ avoid excessive heat

Inactive ingredients

Purified Water, Cocos Nucifera (Coconut oil), Olea Europaea (Olive Oil), Cetyl Alcohol, Glyceryl
stearate, Stearic Acid, Peg 100 stearate,Propanediol, Glycol Distearate,1,2- Hexanediol, Caprylyl
Glycol, Hydroyacetophenone, Citrus Paradisi (Grapefruit) Peel Oil, Citrus Sinensis (Orange) Peel Oil,
Citrus Reticulata (Tangerine) Peel Oil, Hexyldecanol, Bisabolol, Cetylhydroxyproline Palmitamide,
Brassica Campestris (Rapeseed) Sterols, Yeast Ferment Extract, Hydrolyzed Soy Protein, 7-
Dehydrocholestrol, Caprylic/Capric Triglcerides, Glycerin, Phospholipids, Tocopherol Acetate,
Algae Extract, Eugenia Caryophyllus (Clove) Flower Extract, Camellia Sinensis (Green Tea) Leaf
Extract, Isopropyl Myristate, Methyldihydrojasmonate, Ethylene Brassylate, Vanilla Planifolia Extract,
Carthamus Tinctorius (Safflower) Oleosomes, Manuka Honey, Cholecalciferol, Phytonadione, Jojoba
Esters, Zea Mays (Corn) Oil

Silicone Tape

Uses
• To be applied to wounds or scars as a protective silicone barrier.
• As a dressing for abrasions, surgical wounds, donor sites, lacerations, ulcers, skin tears, superficial partial thickness burns, venous leg ulcers.
• As a dressing/securement for IV related uses, pressure ulcers, skin care, and wound care

Precautions
• Do not use if you are allergic to silicone
• Keep out of reach of children

Directions for use
• Apply tape to wound or scar as needed or as directed by your physician. Remove tape, wash area, and apply new tape at least every 24 hours.